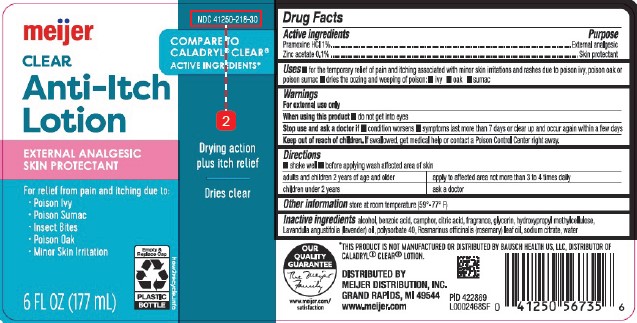 DRUG LABEL: Clear Anti-Itch
NDC: 41250-218 | Form: LOTION
Manufacturer: Meijer, Inc.
Category: otc | Type: HUMAN OTC DRUG LABEL
Date: 20260219

ACTIVE INGREDIENTS: PRAMOXINE HYDROCHLORIDE 10 mg/1 mL; ZINC ACETATE 1 mg/1 mL
INACTIVE INGREDIENTS: ALCOHOL; BENZOIC ACID; CAMPHOR (SYNTHETIC); CITRIC ACID MONOHYDRATE; GLYCERIN; HYPROMELLOSE, UNSPECIFIED; LAVENDER OIL; POLYSORBATE 40; ROSEMARY OIL; SODIUM CITRATE; WATER

Meijer 218.002/218AF
Clear Anti-Itch Lotion

Active ingredients

Pramoxine HCl 1%

Zinc acetate 0.1%

Purpose

External analgesic

Skin protectant

Uses

- for the temporary relief of pain and itching associated with minor skin irritations and rashes due to poison ivy, poison oak or poison sumac
- dries the oozing and weeping of poison: - ivy - oak - sumac

Warnings

For external use only

When using this product

- do not get into eyes

Stop use section and ask a doctor if

- condition worsens
- symptoms last more than 7 days or clear up and occur again within a few days

Keep out of reach of children.

If swallowed, get medical help or contact a Poison Control Center right away.

Directions

- shake well
- before applying wash affected area of skin

adults and children 2 years of age and older - apply to affected area not more than 3 to 4 times daily

children under 2 years - ask a doctor

Other information

store at room temperature (59° - 77° F)

Inactive ingredients

alcohol, benzoic acid, camphor, citric acid, fragrance, glycerin, hydroxypropyl methylcellulose, Lavandula angustifolia (lavender) oil, polysorbate 40, Rosmarinus officinalis (rosemary) leaf oil, sodium citrate, water

disclaimer

*THIS PRODUCT IS NOT MANUFACTURED OR DISTRIBUTED BY BAUSCH HEALTH US, LLC, DISTRIBUTOR OF CALADRYL®CLEAR LOTION.

ADVERSE REACTION

OUR QUALITY GUARANTEE

The Meijer Family

www.meijer.com/satisfaction

DISTRIBUTED BY MEIJER DISTRIBUTION, INC.

GRAND RAPIDS, MI 49544

www.meijer.com

Principal Panel Display

NDC 41250-218-30

Meijer®

Compare to Caladryl®Clear® Active Ingredients*

CLEAR

Anti-Itch

Lotion

External Analgesic/Skin Protectant

Drying Action Plus Itch Relief

Dries Clear

For relief from pain and itching due to:

- Poison Ivy
- Poison Sumac
- Insect Bites
- Poison Oak
- Minor Skin Irritation

Empty & Replace Cap

Plastic Bottle

how2recycle.info

6 FL OZ (177 mL)